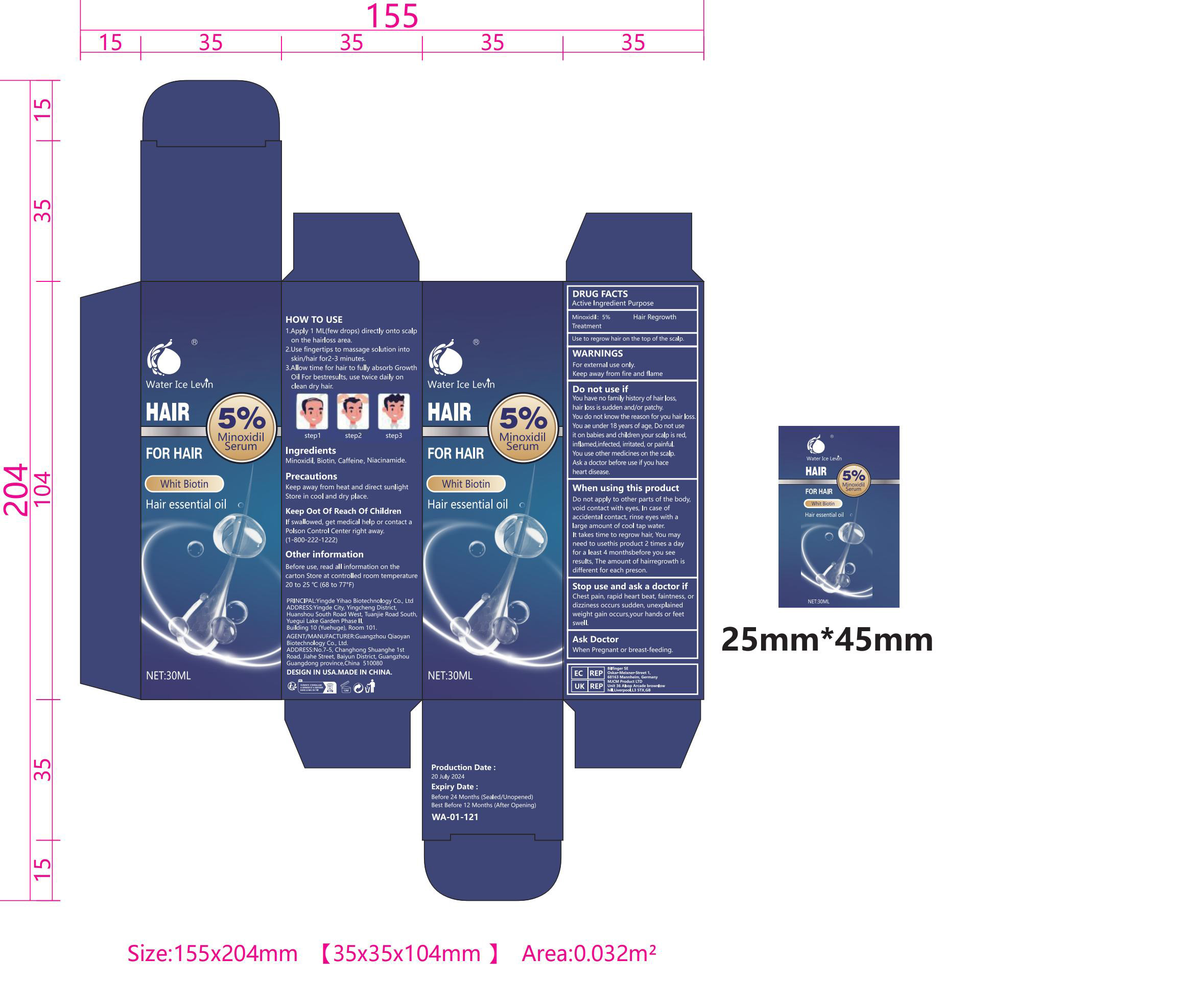 DRUG LABEL: Water Ice Levin Whit Biotin Hair essential oil
NDC: 84550-002 | Form: LIQUID
Manufacturer: Guangzhou Qiaoyan Biotechnology Co., Ltd
Category: otc | Type: HUMAN OTC DRUG LABEL
Date: 20240812

ACTIVE INGREDIENTS: MINOXIDIL 5 g/100 mL
INACTIVE INGREDIENTS: NIACINAMIDE; CAFFEINE; BIOTIN

DRUG FACTSActive Ingredient Purpose

Minoxidil: 5% Treatment
Hair Regrowth

Purpose

Use to regrow hair on the top of the scalp

Purpose

Use to regrow hair on the top of the scalp

Uses

1.Apply 1 ML(few drops) directly onto scalpon the hairloss area.
2.Use fingertips to massage solution intoskin/hair for2-3 minutes.
3.Allow time for hair to fully absorb GrowthOil For bestresults, use twice daily onclean dry hair.

WARNINGS

For external use only.Keep away from fire and flame

Dosage and administration

For external use only.

Do not use if

Do not apply to other parts of the bodyvoid contact with eyes, In case ofaccidental contact, rinse eyes with alarge amount of cool tap water.It takes time to regrow hair, You mayneed to usethis product 2 times a dayfor a least 4 monthsbefore you seeresults, The amount of hairregrowth isdifferent for each preson.

When using this product

Do not apply to other parts of the body,void contact with eyes, In case ofaccidental contact, rinse eyes with alarge amount of cool tap water.It takes time to regrow hair, You mayneed to usethis product 2 times a dayfor a least 4 monthsbefore you seeresults, The amount of hairregrowth isdifferent for each preson.

Stop use and ask a doctor if

Chest pain, rapid heart beat, faintness, ordizziness occurs sudden, unexplainedweight gain occurs,your hands or feetswell.

Keep Oot Of Reach of children

If swallowed, get medical help or contact aPolson Control Center right away.(1-800-222-1222)

Inactive ingredients

Biotin
Caffeine
Niacinamide